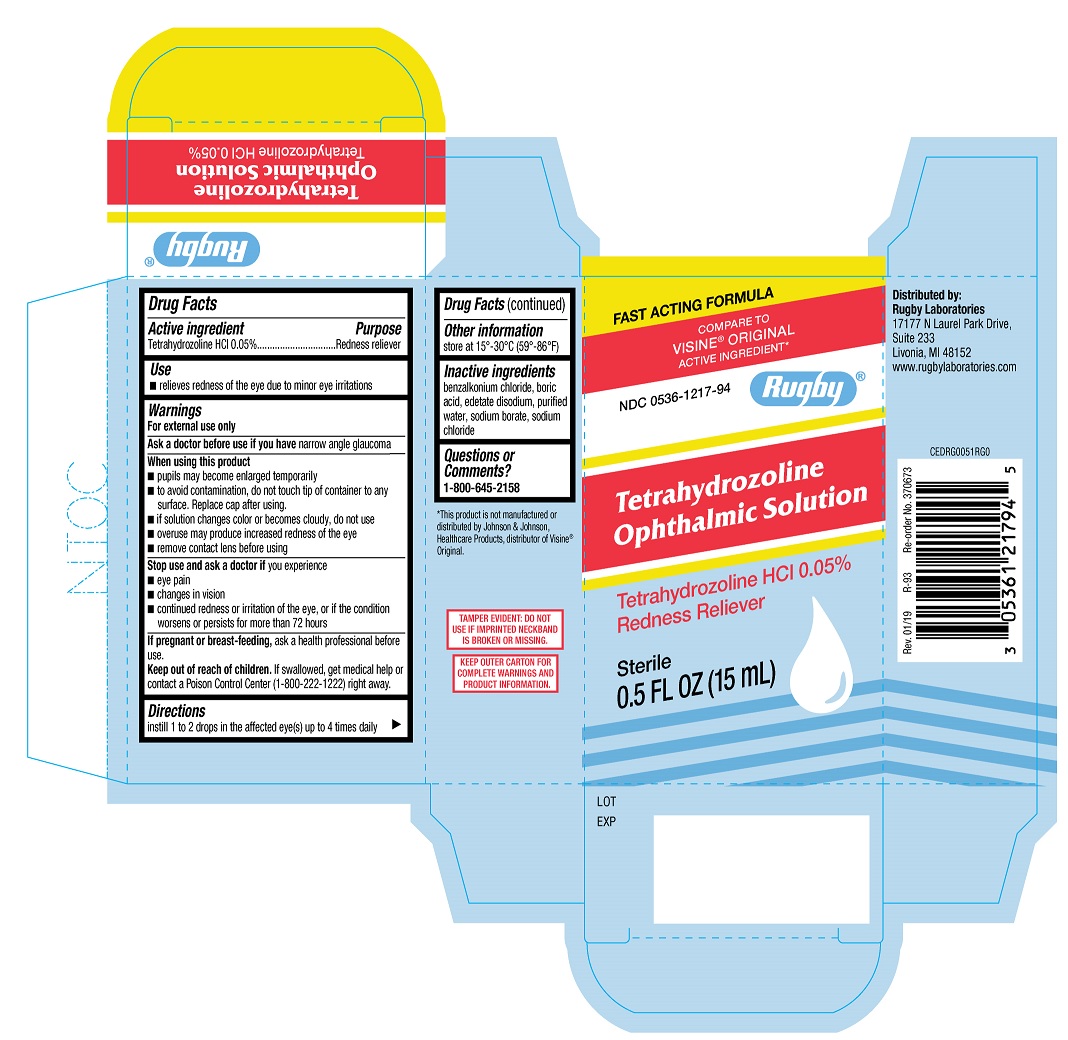 DRUG LABEL: Rugby Tetrahydrozoline Ophthalmic Solution
NDC: 0536-1217 | Form: SOLUTION/ DROPS
Manufacturer: Rugby Laboratories
Category: otc | Type: HUMAN OTC DRUG LABEL
Date: 20231220

ACTIVE INGREDIENTS: TETRAHYDROZOLINE HYDROCHLORIDE 0.05 g/100 mL
INACTIVE INGREDIENTS: SODIUM CHLORIDE; BORIC ACID; WATER; BENZALKONIUM CHLORIDE; EDETATE SODIUM; SODIUM BORATE

Rugby Tetrahydrozoline Ophthalmic Solution (PLD)

Active Ingredient

Tetrahydrozoline HCI 0.05%

Purpose

Redness Reliever

Use

relieves redness in eye due to minor eye irritations

Warnings

For external use only

Warnings

Ask a doctor before use if you have narrow angle glaucoma

Warnings

When using this product

- pupils may become enlarged temporarily
- to avoid contamination, do not touch tip of container to any surface. Replace cap after using.
- if solution changes color or becomes cloudy, do not use
- overuse may produce increased redness of the eye
- remove contact lens before using

Warnings

Stop use and ask a doctor if you experience

- eye pain
- changes in vision
- continued redness or irritation of the eye, or if the condition worsens or persists for more than 72 hours

Warnings

If pregnant or breast-feeding, ask a professional before use.

Warnings

Keep out of reach of children. If swallowed, get medical help or contact Poison Control Center (1-800-222-1222) right away.

Directions

instill 1 to 2 drops in the affected eye(s) up to 4 times daily

Other Information

store at 15°-30°C (59°-86°F)

Inactive ingredients

benzalkonium chloride, boric acid, edetate disodium, purified water, sodium borate, sodium chloride

Questions or Comments?

1-800-645-2158